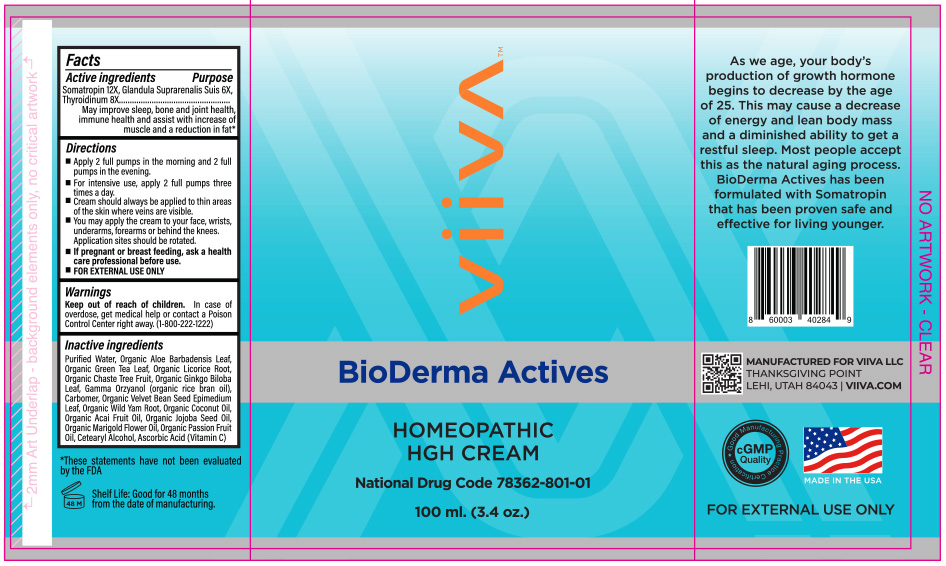 DRUG LABEL: Viiva BioDerma Actives
NDC: 78362-801 | Form: CREAM
Manufacturer: Viiva
Category: homeopathic | Type: HUMAN OTC DRUG LABEL
Date: 20200727

ACTIVE INGREDIENTS: SUS SCROFA ADRENAL GLAND 6 [hp_X]/1 g; THYROID, BOVINE 8 [hp_X]/1 g; SOMATROPIN 12 [hp_X]/1 g
INACTIVE INGREDIENTS: ALOE VERA LEAF; WATER; LICORICE; CHASTE TREE FRUIT; CARBOMER INTERPOLYMER TYPE A (ALLYL SUCROSE CROSSLINKED); GREEN TEA LEAF; GINKGO; GAMMA ORYZANOL; DIOSCOREA VILLOSA ROOT; ACAI OIL; TAGETES MINUTA FLOWER OIL; CETOSTEARYL ALCOHOL; ASCORBIC ACID; MUCUNA PRURIENS SEED; EPIMEDIUM SAGITTATUM TOP; COCONUT OIL; JOJOBA OIL; PASSIFLORA EDULIS FLOWER

ACTIVE INGREDIENTS

Somatropin 12X
Glandula Suprarenalis Suis 6X
Thyroidinum 8X

PURPOSE

As we age, your body's production of growth hormone beings to decrease by the age of 25. This may cause a decrease of energy and lean body mass and a diminished ability to get a restful sleep. Most people accept this as the natural aging process. BioDerma Actives has been formulated with Somatropin that has been proven safe and effective for living younger.

DIRECTIONS

Apply 2 full pumps in the morning and 2 full pumps in the evening; 5 days on, 2 days off. For intensive use, apply 2 full pumps three times a day

INDICATIONS AND USAGE

- Gel should always be applied to thin areas of the skin where veins are visible.
- You may apply the gel to your face, wrists, underarms, forearms or behind the knees. Application sites should be rotated.
- If pregnant or breast feeding, ask a health care professional before use.
- FOR EXTERNAL USE ONLY

INACTIVE INGREDIENTS

Water , Organic Aloe Barbadensis Leaf, Organic Green Tea Leaf, Organic Licorice Root, Orgaic Chaste Tree Fruit, Organic Gingko Biloba Leaf, Gamma Orzyanol (from organic rice bran oil), Carbomer, Organic Velvet Bean Seed, Epimedium Leaf, Organic Wild Yam Root, Organic Coconut Oil, Organic Acai Fruit Oil, Organic Jojoba Seed Oil, Organic Marigold Flower Oil, Organic Passion Fruit Oil, Cetearyl Alcohol, Ascorbic Acid (Vitamin C)

Warnings

In case of overdose, get medical help or contact a Poison Control Center right away. (1-800-222-1222)

Keep out of reach of children